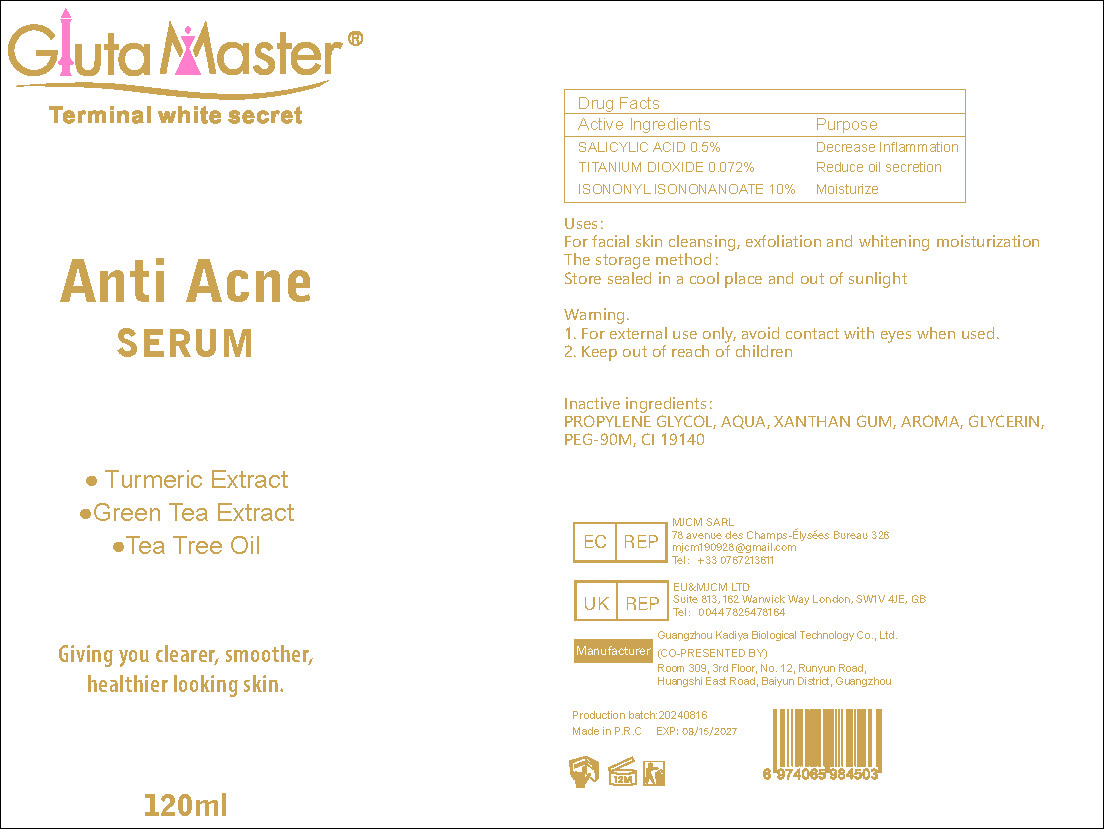 DRUG LABEL: Anti Acne SERUM
NDC: 84423-035 | Form: SOLUTION, CONCENTRATE
Manufacturer: Guangzhou Kadiya Biotechnology Co., Ltd.
Category: otc | Type: HUMAN OTC DRUG LABEL
Date: 20240826

ACTIVE INGREDIENTS: ISONONYL ISONONANOATE 12 mg/120 mL; SALICYLIC ACID 0.6 mg/120 mL; TITANIUM DIOXIDE 0.0864 mg/120 mL
INACTIVE INGREDIENTS: FD&C YELLOW NO. 5; GLYCERIN; WATER; POLYETHYLENE GLYCOL 4000000; XANTHAN GUM; PROPYLENE GLYCOL

Uses：
For the improvement and lightening of redness on the face

INACTIVE INGREDIENT

PROPYLENE GLYCOL、AQUA、XANTHAN GUM、AROMA、GLYCERIN、PEG-90M、CI 19140

WARNINGS

1、For external use only, avoid contact with eyes when used
2、Keep out of reach of children

INDICATIONS AND USAGE

For facial skin cleansing, exfoliation and whitening moisturization

DOSAGE AND ADMINISTRATION

For facial skin cleansing, exfoliation and whitening moisturization

Once in the morning and once in the evening

KEEP OUT OF REACH OF CHILDREN SECTION

Active Ingredients
SALICYLIC ACID 0.5%
TITANIUM DIOXIDE 0.072%
ISONONYL ISONONANOATE 10%

PACKAGE LABEL

Active Ingredients
SALICYLIC ACID 0.5%
TITANIUM DIOXIDE 0.072%
ISONONYL ISONONANOATE 10%
Uses：
For the improvement and lightening of redness on the face
The storage method：
Store sealed in a cool place and out of sunlight

Warning.
1、For external use only, avoid contact with eyes when used
2、Keep out of reach of children

Inactive ingredients：
PROPYLENE GLYCOL、AQUA、XANTHAN GUM、AROMA、GLYCERIN、PEG-90M、CI 19140